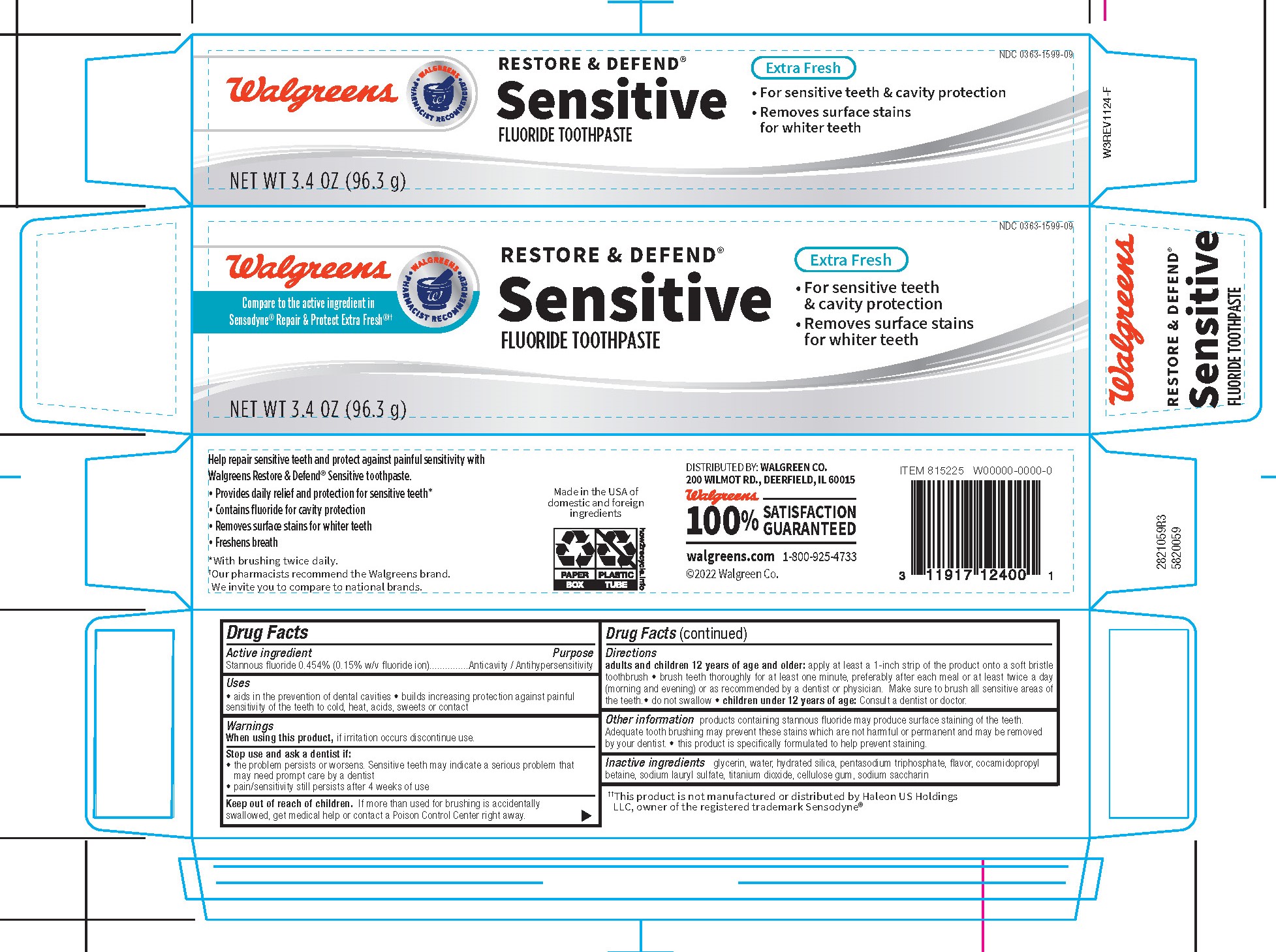 DRUG LABEL: Walgreens Restore and Defend
NDC: 0363-1599 | Form: PASTE, DENTIFRICE
Manufacturer: Walgreens
Category: otc | Type: HUMAN OTC DRUG LABEL
Date: 20251113

ACTIVE INGREDIENTS: STANNOUS FLUORIDE 0.15 g/100 g
INACTIVE INGREDIENTS: COCAMIDOPROPYL BETAINE; WATER; GLYCERIN; SACCHARIN SODIUM; CARBOXYMETHYLCELLULOSE SODIUM; HYDRATED SILICA; SODIUM LAURYL SULFATE; SODIUM TRIPOLYPHOSPHATE ANHYDROUS; TITANIUM DIOXIDE

5820059 Walgreens Sensitive REstore & Defend Whitening (8015223)

ACTIVE INGREDIENT

Stannous fluoride 0.454% w/w (0.15% w/v fluoride ion) .... Anticavity/Antihypersensitivity

INACTIVE INGREDIENT

glycerin, water, hydrated silica, pentasodium triphosphate, flavor, cocamidopropyl betaine, sodium lauryl sulfate, titanium dioxide, cellulose gum, sodium saccharin

INDICATIONS AND USAGE

Adults and children 12 years of age and older: apply at least a 1-inch strip of the produc tonto a soft bristle toothbrush. brush teeth thoroughly for at least one minute, preferably after each meal or at least twice a day (morning and evening) or as recommended by a dentist or physician. Make sure to brush all sensitive areas of the teeth. do not swallow. children under 12 years of age: consult a dentist or doctor.

DOSAGE AND ADMINISTRATION

Aids in the prevention of dental cavities. Builds increasing protection against painful sensitivity of the teeth to cold, heat, acids, sweets or contact.

When using this product, if irritation occurs discontinue use. Stop use and ask a dentist if the problem persists or worsens. Sensitive teeth pay indicate a serious problem that may need prompt care by a dentist. Pain/sensitivity still persists after 4 weeks of use.

Keep out of reach of children. If more than used for bushing is accidentally swallowed, get medical help or contact a poison control center right away.

PURPOSE

Products containing stannous fluoride may produce surface staining of the teeth. Adquate tooth brushing may prevent these stains which are not harmful or permanent and may be removed by your dentist. This product is specifically formulated to help prevent staining. Store below 30C (86F).